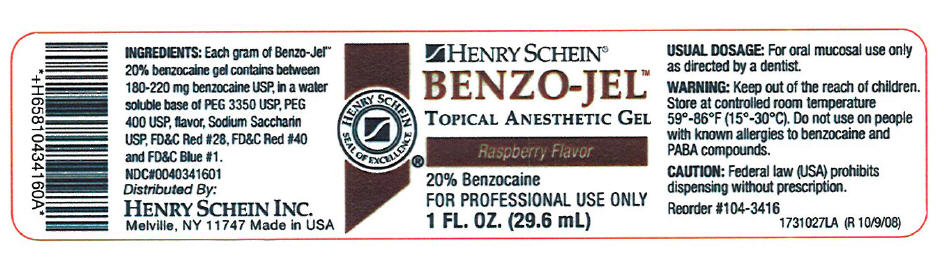 DRUG LABEL: Benzo-Jel 
NDC: 0404-3416 | Form: GEL, DENTIFRICE
Manufacturer: Henry Schein, Inc.
Category: prescription | Type: HUMAN PRESCRIPTION DRUG LABEL
Date: 20100827

ACTIVE INGREDIENTS: Benzocaine 220 mg/1 g

BENZO-JEL™

INGREDIENTS

Each gram of Benzo-Jel™ 20% benzocaine gel contains between 180-220 mg benzocaine USP, in a water soluble base of PEG 3350 USP, PEG 400 USP, flavor, Sodium Saccharin USP, FD&C Red #28, FD&C Red #40 and FD&C Blue #1.

USUAL DOSAGE

For oral mucosal use only as directed by a dentist.

WARNING

Keep out of the reach of children.

STORAGE AND HANDLING

Store at controlled room temperature 59°-86°F (15°-30°C).

Do not use on people with known allergies to benzocaine and PABA compounds.

CAUTION

Federal law (USA) prohibits dispensing without prescription.

Distributed By:
HENRY SCHEIN INC.
Melville, NY 11747

PRINCIPAL DISPLAY PANEL - 29.6 mL Bottle Label

HENRY SCHEIN®

BENZO-JEL™
TOPICAL ANESTHETIC GEL

Raspberry Flavor

20% Benzocaine
FOR PROFESSIONAL USE ONLY
1 FL. OZ. (29.6 mL)